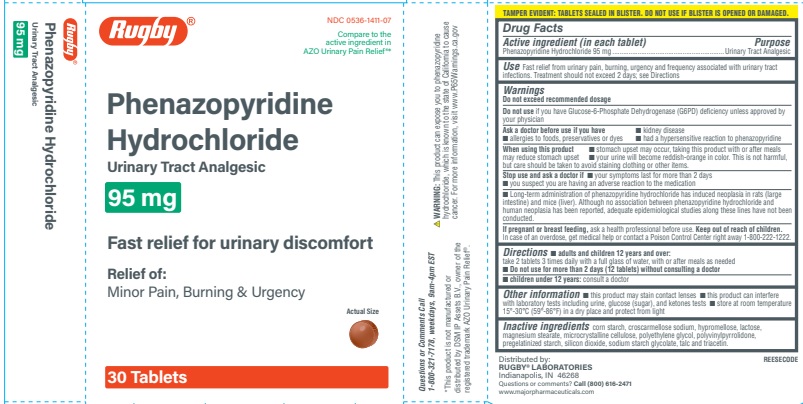 DRUG LABEL: Rugby Phenazopyridine HCl Urinary Tract Analgesic
NDC: 0536-1411 | Form: TABLET
Manufacturer: Rugby Laboratories
Category: otc | Type: HUMAN OTC DRUG LABEL
Date: 20241218

ACTIVE INGREDIENTS: PHENAZOPYRIDINE HYDROCHLORIDE 95 mg/1 1
INACTIVE INGREDIENTS: STARCH, CORN; CELLULOSE, MICROCRYSTALLINE; CROSCARMELLOSE SODIUM; HYPROMELLOSE, UNSPECIFIED; SODIUM STARCH GLYCOLATE TYPE A CORN; LACTOSE; MAGNESIUM STEARATE; POLYETHYLENE GLYCOL, UNSPECIFIED; POVIDONE, UNSPECIFIED; SILICON DIOXIDE; TALC; TRIACETIN

DRUG FACTS

Active Ingredient

Phenazopyridine Hydrochloride 95 mg

Purpose

Urinary Analgesic

Uses

fast relief from urinary pain,burning,urgency and frequency associated with urinary tract infections.

Warning

Do not exceed recommended dosage

Do not use if you have Glucose-6-Phosphate Dehydrogenase (G6PD) deficiency unless approved by your physician

Ask Doctor before use if you have

■ kidney disease
■ allergies to foods, preservatives or dyes
■ had a hypersensitive reaction to Phenazopyridine

■ When using this product stomach upset may occur, taking this product with or after meals may reduce stomach upset
■ your urine will become reddish-orange in color. This is not harmful, but care should be taken to avoid staining clothing or other items.

Stop use and ask a doctor if

■ your symptoms last for more than 2 days
■ you suspect you are having an adverse reaction to the medication

Long-term administration of phenazopyridine hydrochloride has induced neoplasia in rats (large intestine) and mice (liver). Although no association between Phenazopyridine hydrochloride and human neoplasia has been reported, adequate epidemiological studies along these lines have not been conducted.

If pregnant or breast feeding

ask a health professional before use.

Keep out of the reach of children

in case of an overdose,get medical help or contact a Poison Control Center right away 1-800-222-1222.

Directions

■ Adults and children 12 years and over: take 2 tablets 3 times daily with a full glass of water, with or after meals as needed
■ Children under 12 years: consult a doctor
■ Do not use for more than 2 days (12 tablets) without consulting a doctor

Other Information

■ this product may stain contact lenses
■ this product can interfere with laboratory tests including urine, glucose (sugar), and ketones test
■ Store at room temperature 15-30C (59-86°F) in a dry place and protect from light

Inactive Ingredients

lactose, corn starch, croscarmellose sodium, microcrystalline

cellulose, hypromellose, magnesium stearate, polyethylene glycol, polyvinylpyrrolidone, sodium starch glycolate,

pregelatinized starch, silicon dioxide, talc, and triacetin.